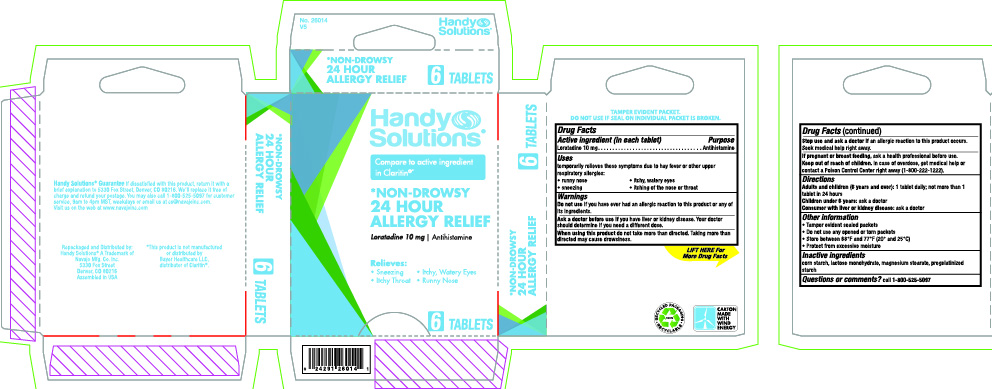 DRUG LABEL: Handy Solutions 24 Hour Allergy
NDC: 67751-163 | Form: TABLET, FILM COATED
Manufacturer: Navajo Manufacturing Company Inc.
Category: otc | Type: HUMAN OTC DRUG LABEL
Date: 20230315

ACTIVE INGREDIENTS: LORATADINE 10 mg/1 1
INACTIVE INGREDIENTS: MAGNESIUM STEARATE; STARCH, CORN; LACTOSE MONOHYDRATE

Handy Solutions 24 Hour Allergy

Active ingredient (in each tablet)

Loratadine 10 mg

Purpose

Antihistamine

Uses

temporarily relieves these symptoms due to hay fever or other upper respiratory allergies:
• runny nose
• itchy, watery eyes
• sneezing
• itching of the nose or throat

Warnings

Do not use

if you have ever had an allergic reaction to this product or any of its ingredients.

Ask a doctor before use if you have

liver or kidney disease. Your doctor should determine if you need a different dose.

When using this product

do not take more than directed. Taking more than directed may cause drowsiness.

Stop use and ask a doctor if

an allergic reaction to this product occurs. Seek medical help right away.

If pregnant or breast-feeding,

ask a health professional before use.

Keep out of reach of children.

In case of overdose, get medical help or contact a Poison Control Center right away.

Directions

Adults and children (12 years and older): 1 tablet daily; not more than 1 tablet in 24 hours

Children under 12 years: do not give to children under 12 years of age

Consumer with liver or kidney disease: ask a doctor before using

Other information

• Tamper evident sealed packets
• Do not use any opened or torn packets
• Store between 68°F and 77°F (20° and 25°C)
• Protect from excessive moisture

Inactive ingredients

corn starch, lactose monohydrate, magnesium stearate, pregelatinized starch

Questions or comments?

call 1-800-525-5097